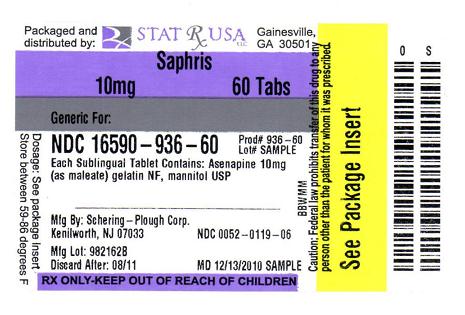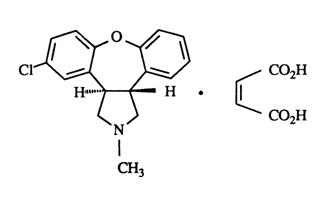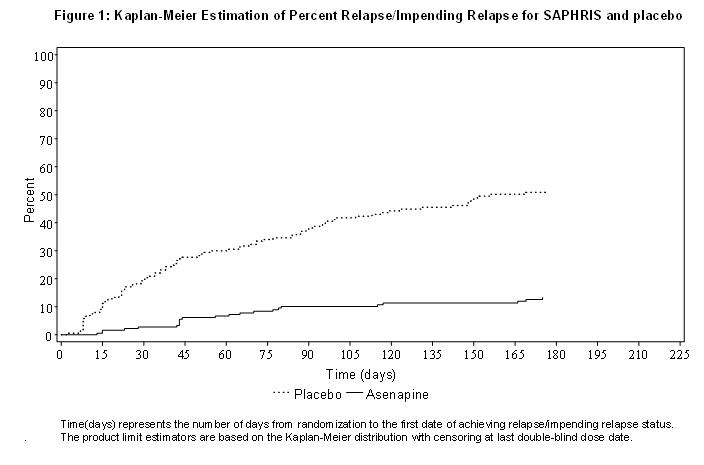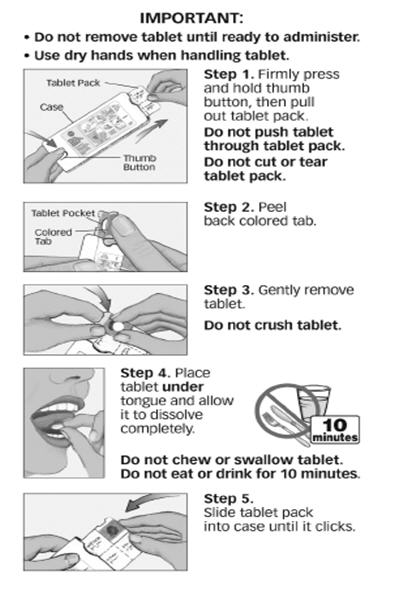 DRUG LABEL: SAPHRIS
NDC: 16590-936 | Form: TABLET
Manufacturer: STAT RX USA LLC
Category: prescription | Type: HUMAN PRESCRIPTION DRUG LABEL
Date: 20110216

ACTIVE INGREDIENTS: ASENAPINE MALEATE 10 mg/1 1
INACTIVE INGREDIENTS: GELATIN; MANNITOL

HIGHLIGHTS OF PRESCRIBING INFORMATION

These highlights do not include all the information needed to use SAPHRIS® (asenapine) safely and effectively. See full prescribing information for SAPHRIS.
SAPHRIS (asenapine) sublingual tablets
Initial U.S. Approval: 2009

WARNING: INCREASED MORTALITY IN ELDERLY PATIENTS WITH DEMENTIA-RELATED PSYCHOSIS

See full prescribing information for complete boxed warning.

Elderly patients with dementia-related psychosis treated with antipsychotic drugs are at an increased risk of death. SAPHRIS is not approved for the treatment of patients with dementia-related psychosis. (5.1)

RECENT MAJOR CHANGES

Indications and Usage, Schizophrenia (1.1) | 09/2010
Indications and Usage, Bipolar Disorder (1.2) | 09/2010
Dosage and Administration, Schizophrenia (2.2) | 09/2010
Dosage and Administration, Bipolar Disorder (2.3) | 09/2010

1 INDICATIONS AND USAGE

SAPHRIS is an atypical antipsychotic indicated for:

- Treatment of schizophrenia. (1.1)
  Efficacy was established in two 6-week clinical trials and one maintenance trial in patients with schizophrenia in adults. (14.1)
- Acute treatment, as monotherapy or adjunctive therapy, of manic or mixed episodes associated with bipolar I disorder. (1.2)
  Efficacy was established in two 3-week monotherapy trials and in one 3-week adjunctive trial in patients with manic or mixed episodes associated with bipolar I disorder in adults. (14.2)

2 DOSAGE AND ADMINISTRATION

 | Starting Dose | Recommended Dose | Maximum Dose
Schizophrenia – acute treatment in adults (2.2) | 5 mg sublingually twice daily | 5 mg sublingually twice daily | 10 mg sublingually twice daily
Schizophrenia – maintenance treatment in adults (2.2) | 5 mg sublingually twice daily for one week | 10 mg sublingually twice daily | 10 mg sublingually twice daily
Bipolar mania – adults: monotherapy (2.3) | 10 mg sublingually twice daily | 5–10 mg sublingually twice daily | 10 mg sublingually twice daily
Bipolar mania – adults: as an adjunct to lithium or valproate (2.3) | 5 mg sublingually twice daily | 5–10 mg sublingually twice daily | 10 mg sublingually twice daily

Administration: Do not swallow tablet. SAPHRIS sublingual tablets should be placed under the tongue and left to dissolve completely. The tablet will dissolve in saliva within seconds. Eating and drinking should be avoided for 10 minutes after administration. (2.1, 17.1)

3 DOSAGE FORMS AND STRENGTHS

Sublingual tablets: 5 mg and 10 mg (3)

Sublingual tablets, black cherry flavor: 5 mg and 10 mg (3)

4 CONTRAINDICATIONS

None (4)

5 WARNINGS AND PRECAUTIONS

- Cerebrovascular Adverse Events: An increased incidence of cerebrovascular adverse events (e.g., stroke, transient ischemic attack) has been seen in elderly patients with dementia-related psychoses treated with atypical antipsychotic drugs. (5.2)
- Neuroleptic Malignant Syndrome: Manage with immediate discontinuation and close monitoring. (5.3)
- Tardive Dyskinesia: Discontinue if clinically appropriate. (5.4)
- Hyperglycemia and Diabetes Mellitus: Monitor patients for symptoms of hyperglycemia including polydipsia, polyuria, polyphagia, and weakness. Monitor glucose regularly in patients with, and at risk for, diabetes. (5.5)
- Weight Gain: Patients should receive regular monitoring of weight. (5.6)
- Orthostatic Hypotension and Syncope: Dizziness, tachycardia or bradycardia, and syncope may occur, especially early in treatment. Use with caution in patients with known cardiovascular or cerebrovascular disease, and in antipsychotic-naïve patients. (5.7)
- Leukopenia, Neutropenia, and Agranulocytosis have been reported with antipsychotics. Patients with a pre-existing low white blood cell count (WBC) or a history of leukopenia/neutropenia should have their complete blood count (CBC) monitored frequently during the first few months of therapy and SAPHRIS should be discontinued at the first sign of a decline in WBC in the absence of other causative factors. (5.8)
- QT Prolongation: Increases in QT interval; avoid use with drugs that also increase the QT interval and in patients with risk factors for prolonged QT interval. (5.9)
- Seizures: Use cautiously in patients with a history of seizures or with conditions that lower the seizure threshold. (5.11)
- Potential for Cognitive and Motor Impairment: Use caution when operating machinery. (5.12)
- Suicide: The possibility of a suicide attempt is inherent in schizophrenia and bipolar disorder. Closely supervise high-risk patients. (5.14)

6 ADVERSE REACTIONS

Commonly observed adverse reactions (incidence ≥5% and at least twice that for placebo) were (6.2):

- Schizophrenia: akathisia, oral hypoesthesia, and somnolence.
- Bipolar Disorder (Monotherapy): somnolence, dizziness, extrapyramidal symptoms other than akathisia, and weight increased.
- Bipolar Disorder (Adjunctive): somnolence and oral hypoesthesia.

To report SUSPECTED ADVERSE REACTIONS, contact Schering Corporation, a subsidiary of Merck & Co., Inc., at 1-800-526-4099 or FDA at 1-800-FDA-1088 or www.fda.gov/medwatch.

7 DRUG INTERACTIONS

- Fluvoxamine (strong CYP1A2 inhibitor) and Paroxetine (CYP2D6 substrate and inhibitor): cautiously approach coadministration with SAPHRIS. (7.1, 7.2)

8 USE IN SPECIFIC POPULATIONS

- Pregnancy: Use SAPHRIS during pregnancy only if the potential benefit justifies the potential risk. (8.1)
- Nursing Mothers: Breast feeding is not recommended. (8.3)
- Pediatric Use: Safety and effectiveness have not been established. (8.4)
- Renal Impairment: No dose adjustment needed. (8.6)
- Hepatic Impairment: SAPHRIS is not recommended in patients with severe hepatic impairment (Child-Pugh C). (2.4, 8.7, 12.3)

FULL PRESCRIBING INFORMATION

WARNING: INCREASED MORTALITY IN ELDERLY PATIENTS WITH DEMENTIA-RELATED PSYCHOSIS

Elderly patients with dementia-related psychosis treated with antipsychotic drugs are at an increased risk of death. Analyses of 17 placebo-controlled trials (modal duration of 10 weeks), largely in patients taking atypical antipsychotic drugs, revealed a risk of death in the drug-treated patients of between 1.6 to 1.7 times that seen in placebo-treated patients. Over the course of a typical 10-week controlled trial, the rate of death in drug-treated patients was about 4.5%, compared to a rate of about 2.6% in the placebo group. Although the causes of death were varied, most of the deaths appeared to be either cardiovascular (e.g., heart failure, sudden death) or infectious (e.g., pneumonia) in nature. Observational studies suggest that, similar to atypical antipsychotic drugs, treatment with conventional antipsychotic drugs may increase mortality. The extent to which the findings of increased mortality in observational studies may be attributed to the antipsychotic drug as opposed to some characteristic(s) of the patients is not clear. SAPHRIS® (asenapine) is not approved for the treatment of patients with dementia-related psychosis [see Warnings and Precautions (5.1)].

1 INDICATIONS AND USAGE

1.1 Schizophrenia

SAPHRIS is indicated for the treatment of schizophrenia. The efficacy of SAPHRIS was established in two 6-week trials and one maintenance trial in adults [see Clinical Studies (14.1)].

1.2 Bipolar Disorder

Monotherapy: SAPHRIS is indicated for the acute treatment of manic or mixed episodes associated with bipolar I disorder. Efficacy was established in two 3-week monotherapy trials in adults [see Clinical Studies (14.2)].

Adjunctive Therapy: SAPHRIS is indicated as adjunctive therapy with either lithium or valproate for the acute treatment of manic or mixed episodes associated with bipolar I disorder. Efficacy was established in one 3-week adjunctive trial in adults [see Clinical Studies (14.2)].

2 DOSAGE AND ADMINISTRATION

2.1 Administration Instructions

SAPHRIS is a sublingual tablet. To ensure optimal absorption, patients should be instructed to place the tablet under the tongue and allow it to dissolve completely. The tablet will dissolve in saliva within seconds. SAPHRIS sublingual tablets should not be crushed, chewed, or swallowed [see Clinical Pharmacology (12.3)]. Patients should be instructed to not eat or drink for 10 minutes after administration [see Clinical Pharmacology (12.3) and Patient Counseling Information (17.1)].

2.2 Schizophrenia

Usual Dose for Acute Treatment in Adults: The recommended starting and target dose of SAPHRIS is 5 mg given twice daily. In short term controlled trials, there was no suggestion of added benefit with a 10 mg twice daily dose, but there was a clear increase in certain adverse reactions. The safety of doses above 10 mg twice daily has not been evaluated in clinical studies.

Maintenance Treatment: Efficacy was demonstrated with SAPHRIS in a maintenance trial in patients with schizophrenia. The starting dose in this study was 5 mg twice daily with an increase up to 10 mg twice daily after 1 week based on tolerability [see Clinical Studies (14.1)]. While there is no body of evidence available to answer the question of how long the schizophrenic patient should remain on SAPHRIS, patients should be periodically reassessed to determine the need for maintenance treatment.

2.3 Bipolar Disorder

Usual Dose for Acute Treatment of Manic or Mixed Episodes Associated with Bipolar I Disorder in Adults:

Monotherapy: The recommended starting dose of SAPHRIS, and the dose maintained by 90% of the patients studied, is 10 mg twice daily. The dose can be decreased to 5 mg twice daily if warranted by adverse effects or based on individual tolerability.

In controlled monotherapy trials, the starting dose for SAPHRIS was 10 mg twice daily. On the second and subsequent days of the trials, the dose could be lowered to 5 mg twice daily, based on tolerability, but less than 10% of patients had their dose reduced. The safety of doses above 10 mg twice daily has not been evaluated in clinical trials.

Adjunctive Therapy: The recommended starting dose of SAPHRIS is 5 mg twice daily when administered as adjunctive therapy with either lithium or valproate. Depending on the clinical response and tolerability in the individual patient, the dose can be increased to 10 mg twice daily. The safety of doses above 10 mg twice daily as adjunctive therapy with lithium or valproate has not been evaluated in clinical trials.

Maintenance Treatment: While there is no body of evidence available to answer the question of how long the bipolar patient should remain on SAPHRIS, whether used as monotherapy or as adjunctive therapy with lithium or valproate, it is generally recommended that responding patients be continued beyond the acute response. If SAPHRIS is used for extended periods in bipolar disorder, the physician should periodically re-evaluate the long-term risks and benefits of the drug for the individual patient.

2.4 Dosage in Special Populations

In a study of subjects with hepatic impairment who were treated with a single dose of SAPHRIS 5 mg, there were increases in asenapine exposures (compared to subjects with normal hepatic function), that correlated with the degree of hepatic impairment. While the results indicated that no dosage adjustments are required in patients with mild (Child-Pugh A) or moderate (Child-Pugh B) hepatic impairment, there was a 7-fold increase (on average) in asenapine concentrations in subjects with severe hepatic impairment (Child-Pugh C) compared to the concentrations of those in subjects with normal hepatic function. Therefore, SAPHRIS is not recommended in patients with severe hepatic impairment [see Use in Special Populations (8.7)]. Dosage adjustments are not routinely required on the basis of age, gender, race, or renal impairment status [see Use in Specific Populations (8.4, 8.5, 8.6) and Clinical Pharmacology (12.3)].

2.5 Switching from Other Antipsychotics

There are no systematically collected data to specifically address switching patients with schizophrenia or bipolar mania from other antipsychotics to SAPHRIS or concerning concomitant administration with other antipsychotics. While immediate discontinuation of the previous antipsychotic treatment may be acceptable for some patients with schizophrenia, more gradual discontinuation may be most appropriate for others. In all cases, the period of overlapping antipsychotic administration should be minimized.

3 DOSAGE FORMS AND STRENGTHS

- SAPHRIS 5-mg tablets are round, white- to off-white sublingual tablets, with "5" on one side.
- SAPHRIS 10-mg tablets are round, white- to off-white sublingual tablets, with "10" on one side.
- SAPHRIS 5-mg tablets, black cherry flavor, are round, white- to off-white sublingual tablets, with "5" on one side within a circle.
- SAPHRIS 10-mg tablets, black cherry flavor, are round, white- to off-white sublingual tablets, with "10" on one side within a circle.

4 CONTRAINDICATIONS

None

5 WARNINGS AND PRECAUTIONS

5.1 Increased Mortality in Elderly Patients with Dementia-Related Psychosis

Elderly patients with dementia-related psychosis treated with antipsychotic drugs are at an increased risk of death. SAPHRIS is not approved for the treatment of patients with dementia-related psychosis [see Boxed Warning].

5.2 Cerebrovascular Adverse Events, Including Stroke, In Elderly Patients with Dementia-Related Psychosis

In placebo-controlled trials with risperidone, aripiprazole, and olanzapine in elderly subjects with dementia, there was a higher incidence of cerebrovascular adverse reactions (cerebrovascular accidents and transient ischemic attacks) including fatalities compared to placebo-treated subjects. SAPHRIS is not approved for the treatment of patients with dementia-related psychosis [see also Boxed Warning and Warnings and Precautions (5.1)].

5.3 Neuroleptic Malignant Syndrome

A potentially fatal symptom complex sometimes referred to as Neuroleptic Malignant Syndrome (NMS) has been reported in association with administration of antipsychotic drugs, including SAPHRIS. Clinical manifestations of NMS are hyperpyrexia, muscle rigidity, altered mental status, and evidence of autonomic instability (irregular pulse or blood pressure, tachycardia, diaphoresis, and cardiac dysrhythmia). Additional signs may include elevated creatine phosphokinase, myoglobinuria (rhabdomyolysis), and acute renal failure.

The diagnostic evaluation of patients with this syndrome is complicated. It is important to exclude cases where the clinical presentation includes both serious medical illness (e.g. pneumonia, systemic infection) and untreated or inadequately treated extrapyramidal signs and symptoms (EPS). Other important considerations in the differential diagnosis include central anticholinergic toxicity, heat stroke, drug fever, and primary central nervous system pathology.

The management of NMS should include: 1) immediate discontinuation of antipsychotic drugs and other drugs not essential to concurrent therapy; 2) intensive symptomatic treatment and medical monitoring; and 3) treatment of any concomitant serious medical problems for which specific treatments are available. There is no general agreement about specific pharmacological treatment regimens for NMS.

If a patient requires antipsychotic drug treatment after recovery from NMS, the potential reintroduction of drug therapy should be carefully considered. The patient should be carefully monitored, since recurrences of NMS have been reported.

5.4 Tardive Dyskinesia

A syndrome of potentially irreversible, involuntary, dyskinetic movements can develop in patients treated with antipsychotic drugs. Although the prevalence of the syndrome appears to be highest among the elderly, especially elderly women, it is impossible to rely upon prevalence estimates to predict, at the inception of antipsychotic treatment, which patients are likely to develop the syndrome. Whether antipsychotic drug products differ in their potential to cause Tardive Dyskinesia (TD) is unknown.

The risk of developing TD and the likelihood that it will become irreversible are believed to increase as the duration of treatment and the total cumulative dose of antipsychotic drugs administered to the patient increase. However, the syndrome can develop, although much less commonly, after relatively brief treatment periods at low doses.

There is no known treatment for established cases of TD, although the syndrome may remit, partially or completely, if antipsychotic treatment is withdrawn. Antipsychotic treatment, itself, however, may suppress (or partially suppress) the signs and symptoms of the syndrome and thereby may possibly mask the underlying process. The effect that symptomatic suppression has upon the long-term course of the syndrome is unknown.

Given these considerations, SAPHRIS should be prescribed in a manner that is most likely to minimize the occurrence of TD. Chronic antipsychotic treatment should generally be reserved for patients who suffer from a chronic illness that (1) is known to respond to antipsychotic drugs, and (2) for whom alternative, equally effective, but potentially less harmful treatments are not available or appropriate. In patients who do require chronic treatment, the smallest dose and the shortest duration of treatment producing a satisfactory clinical response should be sought. The need for continued treatment should be reassessed periodically.

If signs and symptoms of TD appear in a patient on SAPHRIS, drug discontinuation should be considered. However, some patients may require treatment with SAPHRIS despite the presence of the syndrome.

5.5 Hyperglycemia and Diabetes Mellitus

Hyperglycemia, in some cases extreme and associated with ketoacidosis or hyperosmolar coma or death, has been reported in patients treated with atypical antipsychotics. Assessment of the relationship between atypical antipsychotic use and glucose abnormalities is complicated by the possibility of an increased background risk of diabetes mellitus in patients with schizophrenia and the increasing incidence of diabetes mellitus in the general population. Given these confounders, the relationship between atypical antipsychotic use and hyperglycemia-related adverse reactions is not completely understood. However, epidemiological studies suggest an increased risk of treatment-emergent hyperglycemia-related adverse events in patients treated with the atypical antipsychotics included in these studies. Because SAPHRIS was not marketed at the time these studies were performed, it is not known if SAPHRIS is associated with this increased risk. Precise risk estimates for hyperglycemia-related adverse events in patients treated with atypical antipsychotics are not available.

Patients with an established diagnosis of diabetes mellitus who are started on atypical antipsychotics should be monitored regularly for worsening of glucose control. Patients with risk factors for diabetes mellitus (e.g., obesity, family history of diabetes) who are starting treatment with atypical antipsychotics should undergo fasting blood glucose testing at the beginning of treatment and periodically during treatment. Any patient treated with atypical antipsychotics should be monitored for symptoms of hyperglycemia including polydipsia, polyuria, polyphagia, and weakness. Patients who develop symptoms of hyperglycemia during treatment with atypical antipsychotics should undergo fasting blood glucose testing. In some cases, hyperglycemia has resolved when the atypical antipsychotic was discontinued; however, some patients required continuation of anti-diabetic treatment despite discontinuation of the antipsychotic drug.

5.6 Weight Gain

Increases in weight have been observed in pre-marketing clinical trials with SAPHRIS. Patients receiving SAPHRIS should receive regular monitoring of weight [see Patient Counseling Information (17.5)].

In short-term schizophrenia and bipolar mania trials, there were differences in mean weight gain between SAPHRIS-treated and placebo-treated patients. In short-term, placebo-controlled schizophrenia trials, the mean weight gain was 1.1 kg for SAPHRIS-treated patients compared to 0.1 kg for placebo-treated patients. The proportion of patients with a ≥7% increase in body weight (at Endpoint) was 4.9% for SAPHRIS-treated patients versus 2% for placebo-treated patients. In short-term, placebo-controlled bipolar mania trials, the mean weight gain for SAPHRIS-treated patients was 1.3 kg compared to 0.2 kg for placebo-treated patients. The proportion of patients with a ≥7% increase in body weight (at Endpoint) was 5.8% for SAPHRIS-treated patients versus 0.5% for placebo-treated patients.

In a 52-week, double-blind, comparator-controlled trial of patients with schizophrenia or schizoaffective disorder, the mean weight gain from baseline was 0.9 kg. The proportion of patients with a ≥7% increase in body weight (at Endpoint) was 14.7%. Table 1 provides the mean weight change from baseline and the proportion of patients with a weight gain of ≥7% categorized by Body Mass Index (BMI) at baseline:

TABLE 1: Weight Change Results Categorized by BMI at Baseline: Comparator-Controlled 52-Week Study in Schizophrenia
 | BMI <23 SAPHRIS (N=295) | BMI 23 – ≤27 SAPHRIS (N=290) | BMI >27 SAPHRIS (N=302)
Mean change from Baseline (kg) | 1.7 | 1 | 0
% with ≥7% increase in body weight | 22% | 13% | 9%

5.7 Orthostatic Hypotension, Syncope, and Other Hemodynamic Effects

SAPHRIS may induce orthostatic hypotension and syncope in some patients, especially early in treatment, because of its α1-adrenergic antagonist activity. In short-term schizophrenia trials, syncope was reported in 0.2% (1/572) of patients treated with therapeutic doses (5 mg or 10 mg twice daily) of SAPHRIS, compared to 0.3% (1/378) of patients treated with placebo. In short-term bipolar mania trials, syncope was reported in 0.3% (1/379) of patients treated with therapeutic doses (5 mg or 10 mg twice daily) of SAPHRIS, compared to 0% (0/203) of patients treated with placebo. During pre-marketing clinical trials with SAPHRIS, including long-term trials without comparison to placebo, syncope was reported in 0.6% (11/1953) of patients treated with SAPHRIS.

Four normal volunteers in clinical pharmacology studies treated with either intravenous, oral, or sublingual SAPHRIS experienced hypotension, bradycardia, and sinus pauses. These spontaneously resolved in 3 cases, but the fourth subject received external cardiac massage. The risk of this sequence of hypotension, bradycardia, and sinus pause might be greater in nonpsychiatric patients compared to psychiatric patients who are possibly more adapted to certain effects of psychotropic drugs.

Patients should be instructed about nonpharmacologic interventions that help to reduce the occurrence of orthostatic hypotension (e.g., sitting on the edge of the bed for several minutes before attempting to stand in the morning and slowly rising from a seated position). SAPHRIS should be used with caution in (1) patients with known cardiovascular disease (history of myocardial infarction or ischemic heart disease, heart failure or conduction abnormalities), cerebrovascular disease, or conditions which would predispose patients to hypotension (dehydration, hypovolemia, and treatment with antihypertensive medications); and (2) in the elderly. SAPHRIS should be used cautiously when treating patients who receive treatment with other drugs that can induce hypotension, bradycardia, respiratory or central nervous system depression [see Drug Interactions (7)]. Monitoring of orthostatic vital signs should be considered in all such patients, and a dose reduction should be considered if hypotension occurs.

5.8 Leukopenia, Neutropenia, and Agranulocytosis

In clinical trial and postmarketing experience, events of leukopenia/neutropenia have been reported temporally related to antipsychotic agents, including SAPHRIS. Agranulocytosis (including fatal cases) has been reported with other agents in the class.

Possible risk factors for leukopenia/neutropenia include pre-existing low white blood cell count (WBC) and history of drug induced leukopenia/neutropenia. Patients with a pre-existing low WBC or a history of drug induced leukopenia/neutropenia should have their complete blood count (CBC) monitored frequently during the first few months of therapy and SAPHRIS should be discontinued at the first sign of decline in WBC in the absence of other causative factors.

Patients with neutropenia should be carefully monitored for fever or other symptoms or signs of infection and treated promptly if such symptoms or signs occur. Patients with severe neutropenia (absolute neutrophil count <1000/mm^3) should discontinue SAPHRIS and have their WBC followed until recovery.

5.9 QT Prolongation

The effects of SAPHRIS on the QT/QTc interval were evaluated in a dedicated QT study. This trial involved SAPHRIS doses of 5 mg, 10 mg, 15 mg, and 20 mg twice daily, and placebo, and was conducted in 151 clinically stable patients with schizophrenia, with electrocardiographic assessments throughout the dosing interval at baseline and steady state. At these doses, SAPHRIS was associated with increases in QTc interval ranging from 2 to 5 msec compared to placebo. No patients treated with SAPHRIS experienced QTc increases ≥60 msec from baseline measurements, nor did any patient experience a QTc of ≥500 msec.

Electrocardiogram (ECG) measurements were taken at various time points during the SAPHRIS clinical trial program (5 mg or 10 mg twice daily doses). Post-baseline QT prolongations exceeding 500 msec were reported at comparable rates for SAPHRIS and placebo in these short-term trials. There were no reports of Torsade de Pointes or any other adverse reactions associated with delayed ventricular repolarization.

The use of SAPHRIS should be avoided in combination with other drugs known to prolong QTc including Class 1A antiarrhythmics (e.g., quinidine, procainamide) or Class 3 antiarrhythmics (e.g., amiodarone, sotalol), antipsychotic medications (e.g., ziprasidone, chlorpromazine, thioridazine), and antibiotics (e.g., gatifloxacin, moxifloxacin). SAPHRIS should also be avoided in patients with a history of cardiac arrhythmias and in other circumstances that may increase the risk of the occurrence of torsade de pointes and/or sudden death in association with the use of drugs that prolong the QTc interval, including bradycardia; hypokalemia or hypomagnesemia; and presence of congenital prolongation of the QT interval.

5.10 Hyperprolactinemia

Like other drugs that antagonize dopamine D2 receptors, SAPHRIS can elevate prolactin levels, and the elevation can persist during chronic administration. Hyperprolactinemia may suppress hypothalamic GnRH, resulting in reduced pituitary gonadotropin secretion. This, in turn, may inhibit reproductive function by impairing gonadal steroidogenesis in both female and male patients. Galactorrhea, amenorrhea, gynecomastia, and impotence have been reported in patients receiving prolactin-elevating compounds. Long-standing hyperprolactinemia when associated with hypogonadism may lead to decreased bone density in both female and male subjects. In SAPHRIS clinical trials, the incidences of adverse events related to abnormal prolactin levels were 0.4% versus 0% for placebo [see Adverse Reactions (6.2)].

Tissue culture experiments indicate that approximately one-third of human breast cancers are prolactin-dependent in vitro, a factor of potential importance if the prescription of these drugs is considered in a patient with previously-detected breast cancer. Neither clinical studies nor epidemiologic studies conducted to date have shown an association between chronic administration of this class of drugs and tumorigenesis in humans, but the available evidence is too limited to be conclusive.

5.11 Seizures

Seizures were reported in 0% and 0.3% (0/572, 1/379) of patients treated with doses of 5 mg and 10 mg twice daily of SAPHRIS, respectively, compared to 0% (0/503, 0/203) of patients treated with placebo in short-term schizophrenia and bipolar mania trials, respectively. During pre-marketing clinical trials with SAPHRIS, including long-term trials without comparison to placebo, seizures were reported in 0.3% (5/1953) of patients treated with SAPHRIS. As with other antipsychotic drugs, SAPHRIS should be used with caution in patients with a history of seizures or with conditions that potentially lower the seizure threshold, e.g., Alzheimer's dementia. Conditions that lower the seizure threshold may be more prevalent in patients 65 years or older.

5.12 Potential for Cognitive and Motor Impairment

Somnolence was reported in patients treated with SAPHRIS. It was usually transient with the highest incidence reported during the first week of treatment. In short-term, fixed-dose, placebo-controlled schizophrenia trials, somnolence was reported in 15% (41/274) of patients on SAPHRIS 5 mg twice daily and in 13% (26/208) of patients on SAPHRIS 10 mg twice daily compared to 7% (26/378) of placebo patients. In short-term, placebo-controlled bipolar mania trials of therapeutic doses (5–10 mg twice daily), somnolence was reported in 24% (90/379) of patients on SAPHRIS compared to 6% (13/203) of placebo patients. During pre-marketing clinical trials with SAPHRIS, including long-term trials without comparison to placebo, somnolence was reported in 18% (358/1953) of patients treated with SAPHRIS. Somnolence (including sedation) led to discontinuation in 0.6% (12/1953) of patients in short-term, placebo-controlled trials.

Patients should be cautioned about performing activities requiring mental alertness, such as operating hazardous machinery or operating a motor vehicle, until they are reasonably certain that SAPHRIS therapy does not affect them adversely.

5.13 Body Temperature Regulation

Disruption of the body's ability to reduce core body temperature has been attributed to antipsychotic agents. In the short-term placebo-controlled trials for both schizophrenia and acute bipolar disorder, the incidence of adverse reactions suggestive of body temperature increases was low (≤1%) and comparable to placebo. During pre-marketing clinical trials with SAPHRIS, including long-term trials without comparison to placebo, the incidence of adverse reactions suggestive of body temperature increases (pyrexia and feeling hot) was ≤1%. Appropriate care is advised when prescribing SAPHRIS for patients who will be experiencing conditions that may contribute to an elevation in core body temperature, e.g., exercising strenuously, exposure to extreme heat, receiving concomitant medication with anticholinergic activity, or being subject to dehydration.

5.14 Suicide

The possibility of a suicide attempt is inherent in psychotic illnesses and bipolar disorder, and close supervision of high-risk patients should accompany drug therapy. Prescriptions for SAPHRIS should be written for the smallest quantity of tablets consistent with good patient management in order to reduce the risk of overdose.

5.15 Dysphagia

Esophageal dysmotility and aspiration have been associated with antipsychotic drug use. Dysphagia was reported in 0.2% and 0% (1/572, 0/379) of patients treated with therapeutic doses (5–10 mg twice daily) of SAPHRIS as compared to 0% (0/378, 0/203) of patients treated with placebo in short-term schizophrenia and bipolar mania trials, respectively. During pre-marketing clinical trials with SAPHRIS, including long-term trials without comparison to placebo, dysphagia was reported in 0.1% (2/1953) of patients treated with SAPHRIS.

Aspiration pneumonia is a common cause of morbidity and mortality in elderly patients, in particular those with advanced Alzheimer's dementia. SAPHRIS is not indicated for the treatment of dementia-related psychosis, and should not be used in patients at risk for aspiration pneumonia [see also Warnings and Precautions (5.1)].

5.16 Use in Patients with Concomitant Illness

Clinical experience with SAPHRIS in patients with certain concomitant systemic illnesses is limited [see Clinical Pharmacology (12.3)].

SAPHRIS has not been evaluated in patients with a recent history of myocardial infarction or unstable heart disease. Patients with these diagnoses were excluded from pre-marketing clinical trials. Because of the risk of orthostatic hypotension with SAPHRIS, caution should be observed in cardiac patients [see Warnings and Precautions (5.6)].

6 ADVERSE REACTIONS

6.1 Overall Adverse Reactions Profile

The following adverse reactions are discussed in more detail in other sections of the labeling:

- Use in Elderly Patients with Dementia-Related Psychosis [see Boxed Warning and Warnings and Precautions (5.1 and 5.2)]
- Neuroleptic Malignant Syndrome [see Warnings and Precautions (5.3)]
- Tardive Dyskinesia [see Warnings and Precautions (5.4)]
- Hyperglycemia and Diabetes Mellitus [see Warnings and Precautions (5.5)]
- Weight Gain [see Warnings and Precautions (5.6)]
- Orthostatic Hypotension, Syncope, and other Hemodynamic Effects [see Warnings and Precautions (5.7)]
- Leukopenia, Neutropenia, and Agranulocytosis [see Warnings and Precautions (5.8)]
- QT Interval Prolongation [see Warnings and Precautions (5.9)]
- Hyperprolactinemia [see Warnings and Precautions (5.10)]
- Seizures [see Warnings and Precautions (5.11)]
- Potential for Cognitive and Motor Impairment [see Warnings and Precautions (5.12)]
- Body Temperature Regulation [see Warnings and Precautions (5.13)]
- Suicide [see Warnings and Precautions (5.14)]
- Dysphagia [see Warnings and Precautions (5.15)]
- Use in Patients with Concomitant Illness [see Warnings and Precautions (5.16)]

The most common adverse reactions (≥5% and at least twice the rate of placebo) reported with acute treatment in schizophrenia were akathisia, oral hypoesthesia, and somnolence. The safety profile of SAPHRIS in the maintenance treatment of schizophrenia was similar to that seen with acute treatment.

The most common adverse reactions (≥5% and at least twice the rate of placebo) reported with acute monotherapy treatment of manic or mixed episodes associated with bipolar I disorder were somnolence, dizziness, extrapyramidal symptoms other than akathisia, and weight increased and during the adjunctive therapy trial in bipolar disorder were somnolence and oral hypoesthesia.

The information below is derived from a clinical trial database for SAPHRIS consisting of over 4565 patients and/or normal subjects exposed to one or more sublingual doses of SAPHRIS. A total of 1314 SAPHRIS-treated patients were treated for at least 24 weeks and 785 SAPHRIS-treated patients had at least 52 weeks of exposure at therapeutic doses.

The stated frequencies of adverse reactions represent the proportion of individuals who experienced a treatment-emergent adverse event of the type listed. A reaction was considered treatment emergent if it occurred for the first time or worsened while receiving therapy following baseline evaluation.

The figures in the tables and tabulations cannot be used to predict the incidence of side effects in the course of usual medical practice where patient characteristics and other factors differ from those that prevailed in the clinical trials. Similarly, the cited frequencies cannot be compared with figures obtained from other clinical investigations involving different treatment, uses, and investigators. The cited figures, however, do provide the prescriber with some basis for estimating the relative contribution of drug and nondrug factors to the adverse reaction incidence in the population studied.

6.2 Clinical Studies Experience

Adult Patients with Schizophrenia: The following findings are based on the short-term placebo-controlled pre-marketing trials for schizophrenia (a pool of three 6-week fixed-dose trials and one 6-week flexible-dose trial) in which sublingual SAPHRIS was administered in doses ranging from 5 to 10 mg twice daily.

Adverse Reactions Associated with Discontinuation of Treatment: A total of 9% of SAPHRIS-treated subjects and 10% of placebo subjects discontinued due to adverse reactions. There were no drug-related adverse reactions associated with discontinuation in subjects treated with SAPHRIS at the rate of at least 1% and at least twice the placebo rate.

Adverse Reactions Occurring at an Incidence of 2% or More in SAPHRIS-Treated Schizophrenic Patients: Adverse reactions associated with the use of SAPHRIS (incidence of 2% or greater, rounded to the nearest percent, and SAPHRIS incidence greater than placebo) that occurred during acute therapy (up to 6-weeks in patients with schizophrenia) are shown in Table 2.

TABLE 2: Adverse Reactions Reported in 2% or More of Subjects in One of the SAPHRIS Dose Groups and Which Occurred at Greater Incidence Than in the Placebo Group in 6-Week Schizophrenia Trials
System Organ Class / Preferred Term | Placebo | SAPHRIS 5 mg twice daily | SAPHRIS 10 mg twice daily | All SAPHRIS [Also includes the Flexible-dose trial (N=90).] 5 mg or 10 mg twice daily
 | (N=378) | (N=274) | (N=208) | (N=572)
Gastrointestinal disorders
Constipation | 6% | 7% | 4% | 5%
Dry mouth | 1% | 3% | 1% | 2%
Oral hypoesthesia | 1% | 6% | 7% | 5%
Salivary hypersecretion | 0% | <1% | 4% | 2%
Stomach discomfort | 1% | <1% | 3% | 2%
Vomiting | 5% | 4% | 7% | 5%
General disorders
Fatigue | 3% | 4% | 3% | 3%
Irritability | <1% | 2% | 1% | 2%
Investigations
Weight increased | <1% | 2% | 2% | 3%
Metabolism disorders
Increased appetite | <1% | 3% | 0% | 2%
Nervous system disorders
Akathisia [Akathisia includes: akathisia and hyperkinesia.] | 3% | 4% | 11% | 6%
Dizziness | 4% | 7% | 3% | 5%
Extrapyramidal symptoms (excluding akathisia) [Extrapyramidal symptoms included dystonia, oculogyration, dyskinesia, tardive dyskinesia, muscle rigidity, parkinsonism, tremor, and extrapyramidal disorder (excluding akathisia).] | 7% | 9% | 12% | 10%
Somnolence [Somnolence includes the following events: somnolence, sedation, and hypersomnia.] | 7% | 15% | 13% | 13%
Psychiatric disorders
Insomnia | 13% | 16% | 15% | 15%
Vascular disorders
Hypertension | 2% | 2% | 3% | 2%

Dose-Related Adverse Reactions: Of all the adverse reactions listed in Table 2, the only apparent dose-related adverse reaction was akathisia.

Monotherapy in Adult Patients with Bipolar Mania: The following findings are based on the short-term placebo-controlled trials for bipolar mania (a pool of two 3-week flexible-dose trials) in which sublingual SAPHRIS was administered in doses of 5 mg or 10 mg twice daily.

Adverse Reactions Associated with Discontinuation of Treatment: Approximately 10% (38/379) of SAPHRIS-treated patients in short-term, placebo-controlled trials discontinued treatment due to an adverse reaction, compared with about 6% (12/203) on placebo. The most common adverse reactions associated with discontinuation in subjects treated with SAPHRIS (rates at least 1% and at least twice the placebo rate) were anxiety (1.1%) and oral hypoesthesia (1.1%) compared to placebo (0%).

Adverse Reactions Occurring at an Incidence of 2% or More Among SAPHRIS-Treated (Monotherapy) Bipolar Patients: Adverse reactions associated with the use of SAPHRIS (incidence of 2% or greater, rounded to the nearest percent, and SAPHRIS incidence greater than placebo) that occurred during acute monotherapy (up to 3-weeks in patients with bipolar mania) are shown in Table 3.

TABLE 3: Adverse Reactions Reported in 2% or More of Subjects in One of the SAPHRIS Dose Groups and Which Occurred at Greater Incidence Than in the Placebo Group in 3-Week Bipolar Mania Trials
System Organ Class / Preferred Term | Placebo (N=203) | SAPHRIS 5 mg or 10 mg twice daily [SAPHRIS 5 mg to 10 mg twice daily with flexible dosing.] (N=379)
Gastrointestinal disorders
Dry mouth | 1% | 3%
Dyspepsia | 2% | 4%
Oral hypoesthesia | <1% | 4%
Toothache | 2% | 3%
General disorders
Fatigue | 2% | 4%
Investigations
Weight increased | <1% | 5%
Metabolism disorders
Increased appetite | 1% | 4%
Musculoskeletal and connective tissue disorders
Arthralgia | 1% | 3%
Pain in extremity | <1% | 2%
Nervous system disorders
Akathisia | 2% | 4%
Dizziness | 3% | 11%
Dysgeusia | <1% | 3%
Headache | 11% | 12%
Other extrapyramidal symptoms (excluding akathisia) [Extrapyramidal symptoms included: dystonia, blepharospasm, torticollis, dyskinesia, tardive dyskinesia, muscle rigidity, parkinsonism, gait disturbance, masked facies, and tremor (excluding akathisia).] | 2% | 7%
Somnolence [Somnolence includes the following events: somnolence, sedation, and hypersomnia.] | 6% | 24%
Psychiatric disorders
Anxiety | 2% | 4%
Depression | 1% | 2%
Insomnia | 5% | 6%

Adjunctive Therapy in Adult Patients with Bipolar Mania: The following findings are based on a 12 week placebo-controlled trial (with a 3 week efficacy endpoint) in adult patients with bipolar mania in which sublingual SAPHRIS was administered in doses of 5 mg or 10 mg twice daily as adjunctive therapy with lithium or valproate.

Adverse Reactions Associated with Discontinuation of Treatment: Approximately 16% (25/158) of SAPHRIS-treated patients discontinued treatment due to an adverse reaction, compared with about 11% (18/166) on placebo. The most common adverse reactions associated with discontinuation in subjects treated with SAPHRIS (rates at least 1% and at least twice the placebo rate) were depression (2.5%), suicidal ideation (2.5%), bipolar 1 disorder (1.9%), insomnia (1.9%) and depressive symptoms (1.3%).

Adverse Reactions Occurring at an Incidence of 2% or More Among SAPHRIS-Treated (Adjunctive) Bipolar Patients: Adverse reactions associated with the use of SAPHRIS (incidence of 2% or greater, rounded to the nearest percent, and SAPHRIS incidence greater than placebo) that occurred during acute adjunctive therapy at 3 weeks, a time when most of the patients were still participating in the trial, are shown in Table 4.

TABLE 4: Adverse Reactions Reported in 2% or More Among SAPHRIS-Treated (Adjunctive) Bipolar Mania Patients and Which Occurred at Greater Incidence Than in the Placebo Group at 3 Weeks:
System Organ Class / Preferred Term | Placebo (N=166) | SAPHRIS 5 mg or 10 mg twice daily [SAPHRIS 5 mg to 10 mg twice daily with flexible dosing.] (N=158)
Gastrointestinal disorders
Dyspepsia | 2% | 3%
Oral hypoesthesia | 0% | 5%
General disorders
Fatigue | 2% | 4%
Edema peripheral | <1% | 3%
Investigations
Weight increased | 0% | 3%
Nervous system disorders
Dizziness | 2% | 4%
Other extrapyramidal symptoms (excluding akathisia) [Extrapyramidal symptoms included: dystonia, parkinsonism, oculogyration, and tremor (excluding akathisia).] | 5% | 6%
Somnolence [Somnolence includes the following events: somnolence and sedation.] | 10% | 22%
Psychiatric disorders
Insomnia | 8% | 10%
Vascular disorders
Hypertension | <1% | 3%

Dystonia: Antipsychotic Class Effect: Symptoms of dystonia, prolonged abnormal contractions of muscle groups, may occur in susceptible individuals during the first few days of treatment. Dystonic symptoms include: spasm of the neck muscles, sometimes progressing to tightness of the throat, swallowing difficulty, difficulty breathing, and/or protrusion of the tongue. While these symptoms can occur at low doses, they occur more frequently and with greater severity with high potency and at higher doses of first generation antipsychotic drugs. An elevated risk of acute dystonia is observed in males and younger age groups.

Extrapyramidal Symptoms: In the short-term, placebo-controlled schizophrenia and bipolar mania trials, data was objectively collected on the Simpson Angus Rating Scale for extrapyramidal symptoms (EPS), the Barnes Akathisia Scale (for akathisia) and the Assessments of Involuntary Movement Scales (for dyskinesias). The mean change from baseline for the all-SAPHRIS 5 mg or 10 mg twice daily treated group was comparable to placebo in each of the rating scale scores.

In the short-term, placebo-controlled schizophrenia trials, the incidence of reported EPS-related events, excluding events related to akathisia, for SAPHRIS-treated patients was 10% versus 7% for placebo; and the incidence of akathisia-related events for SAPHRIS-treated patients was 6% versus 3% for placebo. In short-term placebo-controlled bipolar mania trials, the incidence of EPS-related events, excluding events related to akathisia, for SAPHRIS-treated patients was 7% versus 2% for placebo; and the incidence of akathisia-related events for SAPHRIS-treated patients was 4% versus 2% for placebo.

Laboratory Test Abnormalities:

Glucose: The effects on fasting serum glucose levels in the short-term schizophrenia and bipolar mania trials revealed no clinically relevant mean changes [see also Warnings and Precautions (5.5)]. In the short-term placebo-controlled schizophrenia trials, the mean increase in fasting glucose levels for SAPHRIS-treated patients was 3.2 mg/dL compared to a decrease of 1.6 mg/dL for placebo-treated patients. The proportion of patients with fasting glucose elevations ≥126 mg/dL (at Endpoint), was 7.4% for SAPHRIS-treated patients versus 6% for placebo-treated patients. In the short-term, placebo-controlled bipolar mania trials, the mean decreases in fasting glucose levels for both SAPHRIS-treated and placebo-treated patients were 0.6 mg/dL. The proportion of patients with fasting glucose elevations ≥126 mg/dL (at Endpoint), was 4.9% for SAPHRIS-treated patients versus 2.2% for placebo-treated patients.

In a 52-week, double-blind, comparator-controlled trial of patients with schizophrenia and schizoaffective disorder, the mean increase from baseline of fasting glucose was 2.4 mg/dL.

Lipids: The effects on total cholesterol and fasting triglycerides in the short-term schizophrenia and bipolar mania trials revealed no clinically relevant mean changes. In short-term, placebo-controlled schizophrenia trials, the mean increase in total cholesterol levels for SAPHRIS-treated patients was 0.4 mg/dL compared to a decrease of 3.6 mg/dL for placebo-treated patients. The proportion of patients with total cholesterol elevations ≥240 mg/dL (at Endpoint) was 8.3% for SAPHRIS-treated patients versus 7% for placebo-treated patients. In short-term, placebo-controlled bipolar mania trials, the mean increase in total cholesterol levels for SAPHRIS-treated patients was 1.1 mg/dL compared to a decrease of 1.5 mg/dL in placebo-treated patients. The proportion of patients with total cholesterol elevations ≥240 mg/dL (at Endpoint) was 8.7% for SAPHRIS-treated patients versus 8.6% for placebo-treated patients. In short-term, placebo-controlled schizophrenia trials, the mean increase in triglyceride levels for SAPHRIS-treated patients was 3.8 mg/dL compared to a decrease of 13.5 mg/dL for placebo-treated patients. The proportion of patients with elevations in triglycerides ≥200 mg/dL (at Endpoint) was 13.2% for SAPHRIS-treated patients versus 10.5% for placebo-treated patients. In short-term, placebo-controlled bipolar mania trials, the mean decrease in triglyceride levels for SAPHRIS-treated patients was 3.5 mg/dL versus 17.9 mg/dL for placebo-treated subjects. The proportion of patients with elevations in triglycerides ≥200 mg/dL (at Endpoint) was 15.2% for SAPHRIS-treated patients versus 11.4% for placebo-treated patients.

In a 52-week, double-blind, comparator-controlled trial of patients with schizophrenia and schizoaffective disorder, the mean decrease from baseline of total cholesterol was 6 mg/dL and the mean decrease from baseline of fasting triglycerides was 9.8 mg/dL.

Transaminases: Transient elevations in serum transaminases (primarily ALT) in the short-term schizophrenia and bipolar mania trials were more common in treated patients but mean changes were not clinically relevant. In short-term, placebo-controlled schizophrenia trials, the mean increase in transaminase levels for SAPHRIS-treated patients was 1.6 units/L compared to a decrease of 0.4 units/L for placebo-treated patients. The proportion of patients with transaminase elevations ≥3 times ULN (at Endpoint) was 0.9% for SAPHRIS-treated patients versus 1.3% for placebo-treated patients. In short-term, placebo-controlled bipolar mania trials, the mean increase in transaminase levels for SAPHRIS-treated patients was 8.9 units/L compared to a decrease of 4.9 units/L in placebo-treated patients. The proportion of patients with transaminase elevations ≥3 times upper limit of normal (ULN) (at Endpoint) was 2.5% for SAPHRIS-treated patients versus 0.6% for placebo-treated patients. No cases of more severe liver injury were seen.

In a 52-week, double-blind, comparator-controlled trial of patients with schizophrenia and schizoaffective disorder, the mean increase from baseline of ALT was 1.7 units/L.

Prolactin: The effects on prolactin levels in the short-term schizophrenia and bipolar mania trials revealed no clinically relevant mean changes in baseline. In short-term, placebo-controlled schizophrenia trials, the mean decreases in prolactin levels were 6.5 ng/mL for SAPHRIS-treated patients compared to 10.7 ng/mL for placebo-treated patients. The proportion of patients with prolactin elevations ≥4 times ULN (at Endpoint) were 2.6% for SAPHRIS-treated patients versus 0.6% for placebo-treated patients. In short-term, placebo-controlled bipolar mania trials, the mean increase in prolactin levels was 4.9 ng/mL for SAPHRIS-treated patients compared to a decrease of 0.2 ng/mL for placebo-treated patients. The proportion of patients with prolactin elevations ≥4 times ULN (at Endpoint) were 2.3% for SAPHRIS-treated patients versus 0.7% for placebo-treated patients.

In a long-term (52-week), double-blind, comparator-controlled trial of patients with schizophrenia and schizoaffective disorder, the mean decrease in prolactin from baseline for SAPHRIS-treated patients was 26.9 ng/mL.

Creatine Kinase (CK): The proportion of patients with CK elevations >3 times ULN at any time were 6.4% and 11.1% for patients treated with SAPHRIS 5 mg bid and 10 mg bid, respectively, as compared to 6.7% for placebo-treated patients in short-term, fixed-dose trials in schizophrenia and bipolar mania. The clinical relevance of this finding is unknown.

Other Adverse Reactions Observed During the Premarketing Evaluation of SAPHRIS: Following is a list of MedDRA terms that reflect adverse reactions reported by patients treated with sublingual SAPHRIS at multiple doses of ≥5 mg twice daily during any phase of a trial within the database of adult patients. The reactions listed are those that could be of clinical importance, as well as reactions that are plausibly drug-related on pharmacologic or other grounds. Reactions already listed in other parts of Adverse Reactions (6), or those considered in Warnings and Precautions (5) or Overdosage (10) are not included. Although the reactions reported occurred during treatment with SAPHRIS, they were not necessarily caused by it. Reactions are further categorized by MedDRA system organ class and listed in order of decreasing frequency according to the following definitions: those occurring in at least 1/100 patients (only those not already listed in the tabulated results from placebo-controlled trials appear in this listing); those occurring in 1/100 to 1/1000 patients; and those occurring in fewer than 1/1000 patients.

Blood and lymphatic disorders: <1/1000 patients: thrombocytopenia; ≥1/1000 patients and <1/100 patients: anemia
Cardiac disorders: ≥1/1000 patients and <1/100 patients: tachycardia, temporary bundle branch block
Eye disorders: ≥1/1000 patients and <1/100 patients: accommodation disorder
Gastrointestinal disorders: ≥1/1000 patients and <1/100 patients: oral paraesthesia, glossodynia, swollen tongue
General disorders: <1/1000 patients: idiosyncratic drug reaction
Investigations: ≥1/1000 patients and <1/100 patients: hyponatremia
Nervous system disorders: ≥1/1000 patients and <1/100 patients: dysarthria

6.3 Postmarketing Experience

Adverse reactions have been identified during postapproval use of SAPHRIS. Because these reactions are reported voluntarily from a population of uncertain size, it is generally not possible to reliably estimate their frequency or establish a causal relationship to drug exposure.

There have been postmarketing reports of serious hypersensitivity reactions in patients treated with SAPHRIS, including swollen tongue and swollen throat (pharyngeal edema). The local anesthetic properties of asenapine should be considered as a possible alternative etiology for the oropharyngeal symptoms.

7 DRUG INTERACTIONS

The risks of using SAPHRIS in combination with other drugs have not been extensively evaluated. Given the primary CNS effects of SAPHRIS, caution should be used when it is taken in combination with other centrally-acting drugs or alcohol.

Because of its α1-adrenergic antagonism with potential for inducing hypotension, SAPHRIS may enhance the effects of certain antihypertensive agents.

7.1 Potential for Other Drugs to Affect SAPHRIS

Asenapine is cleared primarily through direct glucuronidation by UGT1A4 and oxidative metabolism by cytochrome P450 isoenzymes (predominantly CYP1A2). The potential effects of inhibitors of several of these enzyme pathways on asenapine clearance were studied.

TABLE 5: Summary of Effect of Coadministered Drugs on Exposure to Asenapine in Healthy Volunteers
Coadministered drug (Postulated effect on CYP450/UGT) | Dose schedules |  | Effect on asenapine pharmacokinetics |  | Recommendation
Coadministered drug (Postulated effect on CYP450/UGT) | Coadministered drug | Asenapine | Cmax | AUC0–∞
Fluvoxamine (CYP1A2 inhibitor) | 25 mg twice daily for 8 days | 5 mg Single Dose | +13% | +29% | Coadminister with caution [The full therapeutic dose of fluvoxamine would be expected to cause a greater increase in asenapine plasma concentrations. AUC: Area under the curve.]
Paroxetine (CYP2D6 inhibitor) | 20 mg once daily for 9 days | 5 mg Single Dose | –13% | –9% | No SAPHRIS dose adjustment required [see Drug Interactions (7.2)]
Imipramine (CYP1A2/2C19/3A4 inhibitor) | 75 mg Single Dose | 5 mg Single Dose | +17% | +10% | No SAPHRIS dose adjustment required
Cimetidine (CYP3A4/2D6/1A2 inhibitor) | 800 mg twice daily for 8 days | 5 mg Single Dose | –13% | +1% | No SAPHRIS dose adjustment required
Carbamazepine (CYP3A4 inducer) | 400 mg twice daily for 15 days | 5 mg Single Dose | –16% | –16% | No SAPHRIS dose adjustment required
Valproate (UGT1A4 inhibitor) | 500 mg twice daily for 9 days | 5 mg Single Dose | 2% | –1% | No SAPHRIS dose adjustment required

A population pharmacokinetic analysis indicated that the concomitant administration of lithium had no effect on the pharmacokinetics of asenapine.

7.2 Potential for SAPHRIS to Affect Other Drugs

Coadministration with CYP2D6 Substrates: In vitro studies indicate that asenapine weakly inhibits CYP2D6.

Following coadministration of dextromethorphan and SAPHRIS in healthy subjects, the ratio of dextrorphan/dextromethorphan (DX/DM) as a marker of CYP2D6 activity was measured. Indicative of CYP2D6 inhibition, treatment with SAPHRIS 5 mg twice daily decreased the DX/DM ratio to 0.43. In the same study, treatment with paroxetine 20 mg daily decreased the DX/DM ratio to 0.032. In a separate study, coadministration of a single 75-mg dose of imipramine with a single 5-mg dose of SAPHRIS did not affect the plasma concentrations of the metabolite desipramine (a CYP2D6 substrate). Thus, in vivo, SAPHRIS appears to be at most a weak inhibitor of CYP2D6. Coadministration of a single 20-mg dose of paroxetine (a CYP2D6 substrate and inhibitor) during treatment with 5 mg SAPHRIS twice daily in 15 healthy male subjects resulted in an almost 2-fold increase in paroxetine exposure. Asenapine may enhance the inhibitory effects of paroxetine on its own metabolism.

SAPHRIS should be coadministered cautiously with drugs that are both substrates and inhibitors for CYP2D6.

Valproic acid and lithium pre-dose serum concentrations collected from an adjunctive therapy study were comparable between asenapine treated patients and placebo treated patients indicating a lack of effect of asenapine on valproic and lithium plasma levels.

8 USE IN SPECIFIC POPULATIONS

8.1 Pregnancy

TERATOGENIC EFFECTS

Pregnancy Category C: There are no adequate and well-controlled studies of SAPHRIS in pregnant women.

In animal studies, asenapine increased post-implantation loss and decreased pup weight and survival at doses similar to or less than recommended clinical doses. In these studies there was no increase in the incidence of structural abnormalities caused by asenapine.

Asenapine was not teratogenic in reproduction studies in rats and rabbits at intravenous doses up to 1.5 mg/kg in rats and 0.44 mg/kg in rabbits. These doses are 0.7 and 0.4 times, respectively, the maximum recommended human dose (MRHD) of 10 mg twice daily given sublingually on a mg/m2 basis. Plasma levels of asenapine were measured in the rabbit study, and the area under the curve (AUC) at the highest dose tested was 2 times that in humans receiving the MRHD.

In a study in which rats were treated from day 6 of gestation through day 21 postpartum with intravenous doses of asenapine of 0.3, 0.9, and 1.5 mg/kg/day (0.15, 0.4, and 0.7 times the MRHD of 10 mg twice daily given sublingually on a mg/m2 basis), increases in post-implantation loss and early pup deaths were seen at all doses, and decreases in subsequent pup survival and weight gain were seen at the two higher doses. A cross-fostering study indicated that the decreases in pup survival were largely due to prenatal drug effects. Increases in post-implantation loss and decreases in pup weight and survival were also seen when pregnant rats were dosed orally with asenapine.

Non-teratogenic Effects

Neonates exposed to antipsychotic drugs during the third trimester of pregnancy are at risk for extrapyramidal and/or withdrawal symptoms following delivery. There have been reports of agitation, hypertonia, hypotonia, tremor, somnolence, respiratory distress and feeding disorder in these neonates. These complications have varied in severity; while in some cases symptoms have been self-limited, in other cases neonates have required intensive care unit support and prolonged hospitalization. SAPHRIS (asenapine) should be used during pregnancy only if the potential benefit justifies the potential risk to the fetus.

8.2 Labor and Delivery

The effect of SAPHRIS on labor and delivery in humans is unknown.

8.3 Nursing Mothers

Asenapine is excreted in milk of rats during lactation. It is not known whether asenapine or its metabolites are excreted in human milk. Because many drugs are excreted in human milk, caution should be exercised when SAPHRIS is administered to a nursing woman. It is recommended that women receiving SAPHRIS should not breast feed.

8.4 Pediatric Use

Safety and effectiveness in pediatric patients have not been established.

8.5 Geriatric Use

Clinical studies of SAPHRIS in the treatment of schizophrenia and bipolar mania did not include sufficient numbers of patients aged 65 and over to determine whether or not they respond differently than younger patients. Of the approximately 2250 patients in pre-marketing clinical studies of SAPHRIS, 1.1% (25) were 65 years of age or over. Multiple factors that might increase the pharmacodynamic response to SAPHRIS, causing poorer tolerance or orthostasis, could be present in elderly patients, and these patients should be monitored carefully.

Elderly patients with dementia-related psychosis treated with SAPHRIS are at an increased risk of death compared to placebo. SAPHRIS is not approved for the treatment of patients with dementia-related psychosis [see Boxed Warning].

8.6 Renal Impairment

The exposure of asenapine following a single dose of 5 mg was similar among subjects with varying degrees of renal impairment and subjects with normal renal function [see Clinical Pharmacology (12.3)].

8.7 Hepatic Impairment

In subjects with severe hepatic impairment who were treated with a single dose of SAPHRIS 5 mg, asenapine exposures (on average), were 7-fold higher than the exposures observed in subjects with normal hepatic function. Thus, SAPHRIS is not recommended in patients with severe hepatic impairment (Child-Pugh C) [see Dosage and Administration (2.4) and Clinical Pharmacology (12.3)].

9 DRUG ABUSE AND DEPENDENCE

9.1 Controlled Substance

SAPHRIS is not a controlled substance.

9.2 Abuse

SAPHRIS has not been systematically studied in animals or humans for its abuse potential or its ability to induce tolerance or physical dependence. Thus, it is not possible to predict the extent to which a CNS-active drug will be misused, diverted and/or abused once it is marketed. Patients should be evaluated carefully for a history of drug abuse, and such patients should be observed carefully for signs that they are misusing or abusing SAPHRIS (e.g., drug-seeking behavior, increases in dose).

10 OVERDOSAGE

Human Experience: In pre-marketing clinical studies involving more than 3350 patients and/or healthy subjects, accidental or intentional acute overdosage of SAPHRIS was identified in 3 patients. Among these few reported cases of overdose, the highest estimated ingestion of SAPHRIS was 400 mg. Reported adverse reactions at the highest dosage included agitation and confusion.

Management of Overdosage: There is no specific antidote to SAPHRIS. The possibility of multiple drug involvement should be considered. An electrocardiogram should be obtained and management of overdose should concentrate on supportive therapy, maintaining an adequate airway, oxygenation and ventilation, and management of symptoms.

Hypotension and circulatory collapse should be treated with appropriate measures, such as intravenous fluids and/or sympathomimetic agents (epinephrine and dopamine should not be used, since beta stimulation may worsen hypotension in the setting of SAPHRIS-induced alpha blockade). In case of severe extrapyramidal symptoms, anticholinergic medication should be administered. Close medical supervision and monitoring should continue until the patient recovers.

11 DESCRIPTION

SAPHRIS is a psychotropic agent that is available for sublingual administration. Asenapine belongs to the class dibenzo-oxepino pyrroles. The chemical designation is (3aRS,12bRS)-5-Chloro-2-methyl-2,3,3a,12b-tetrahydro-1Hdibenzo[2,3:6,7]oxepino[4,5-c]pyrrole (2Z)-2-butenedioate (1:1). Its molecular formula is C17H16ClNO•C4H4O4 and its molecular weight is 401.84 (free base: 285.8). The chemical structure is:

Asenapine is a white- to off-white powder.

SAPHRIS is supplied for sublingual administration in tablets containing 5-mg or 10-mg asenapine; inactive ingredients include gelatin and mannitol.

SAPHRIS, black cherry flavor, is supplied for sublingual administration in tablets containing 5-mg or 10-mg asenapine; inactive ingredients include gelatin, mannitol, sucralose, and black cherry flavor.

12 CLINICAL PHARMACOLOGY

12.1 Mechanism of Action

The mechanism of action of asenapine, as with other drugs having efficacy in schizophrenia and bipolar disorder, is unknown. It has been suggested that the efficacy of asenapine in schizophrenia is mediated through a combination of antagonist activity at D2 and 5-HT2A receptors.

12.2 Pharmacodynamics

Asenapine exhibits high affinity for serotonin 5-HT1A, 5-HT1B, 5-HT2A, 5-HT2B, 5-HT2C, 5-HT5, 5-HT6, and 5-HT7 receptors (Ki values of 2.5, 4.0, 0.06, 0.16, 0.03, 1.6, 0.25, and 0.13 nM), dopamine D2, D3, D4, and D1 receptors (Ki values of 1.3, 0.42, 1.1, and 1.4 nM), α1 and α2-adrenergic receptors (Ki values of 1.2 and 1.2 nM), and histamine H1 receptors (Ki value 1.0 nM), and moderate affinity for H2 receptors (Ki value of 6.2 nM). In in vitro assays asenapine acts as an antagonist at these receptors. Asenapine has no appreciable affinity for muscarinic cholinergic receptors (e.g., Ki value of 8128 nM for M1).

12.3 Pharmacokinetics

Following a single 5-mg dose of SAPHRIS, the mean Cmax was approximately 4 ng/mL and was observed at a mean tmax of 1 hour. Elimination of asenapine is primarily through direct glucuronidation by UGT1A4 and oxidative metabolism by cytochrome P450 isoenzymes (predominantly CYP1A2). Following an initial more rapid distribution phase, the mean terminal half-life is approximately 24 hrs. With multiple-dose twice-daily dosing, steady-state is attained within 3 days. Overall, steady-state asenapine pharmacokinetics are similar to single-dose pharmacokinetics.

Absorption: Following sublingual administration, asenapine is rapidly absorbed with peak plasma concentrations occurring within 0.5 to 1.5 hours. The absolute bioavailability of sublingual asenapine at 5 mg is 35%. Increasing the dose from 5 mg to 10 mg twice daily (a two-fold increase) results in less than linear (1.7 times) increases in both the extent of exposure and maximum concentration. The absolute bioavailability of asenapine when swallowed is low (<2% with an oral tablet formulation).

The intake of water several (2 or 5) minutes after asenapine administration resulted in decreased asenapine exposure. Therefore, eating and drinking should be avoided for 10 minutes after administration [see Dosage and Administration (2.1)].

Distribution: Asenapine is rapidly distributed and has a large volume of distribution (approximately 20 – 25 L/kg), indicating extensive extravascular distribution. Asenapine is highly bound (95%) to plasma proteins, including albumin and α1-acid glycoprotein.

Metabolism and Elimination: Direct glucuronidation by UGT1A4 and oxidative metabolism by cytochrome P450 isoenzymes (predominantly CYP1A2) are the primary metabolic pathways for asenapine.

Asenapine is a high clearance drug with a clearance after intravenous administration of 52 L/h. In this circumstance, hepatic clearance is influenced primarily by changes in liver blood flow rather than by changes in the intrinsic clearance, i.e., the metabolizing enzymatic activity. Following an initial more rapid distribution phase, the terminal half life of asenapine is approximately 24 hours. Steady-state concentrations of asenapine are reached within 3 days of twice daily dosing.

After administration of a single dose of [^14C]-labeled asenapine, about 90% of the dose was recovered; approximately 50% was recovered in urine, and 40% recovered in feces. About 50% of the circulating species in plasma have been identified. The predominant species was asenapine N^+-glucuronide; others included N-desmethylasenapine, N-desmethylasenapine N-carbamoyl glucuronide, and unchanged asenapine in smaller amounts. SAPHRIS activity is primarily due to the parent drug.

In vitro studies indicate that asenapine is a substrate for UGT1A4, CYP1A2 and to a lesser extent CYP3A4 and CYP2D6. Asenapine is a weak inhibitor of CYP2D6. Asenapine does not cause induction of CYP1A2 or CYP3A4 activities in cultured human hepatocytes. Coadministration of asenapine with known inhibitors, inducers or substrates of these metabolic pathways has been studied in a number of drug-drug interaction studies [see Drug Interactions (7)].

Smoking: A population pharmacokinetic analysis indicated that smoking, which induces CYP1A2, had no effect on the clearance of asenapine in smokers. In a crossover study in which 24 healthy male subjects (who were smokers) were administered a single 5-mg sublingual dose, concomitant smoking had no effect on the pharmacokinetics of asenapine.

Food: A crossover study in 26 healthy male subjects was performed to evaluate the effect of food on the pharmacokinetics of a single 5-mg dose of asenapine. Consumption of food immediately prior to sublingual administration decreased asenapine exposure by 20%; consumption of food 4 hours after sublingual administration decreased asenapine exposure by about 10%. These effects are probably due to increased hepatic blood flow.

In clinical trials establishing the efficacy and safety of SAPHRIS, patients were instructed to avoid eating for 10 minutes following sublingual dosing. There were no other restrictions with regard to the timing of meals in these trials [see Dosage and Administration (2.1) and Patient Counseling Information (17.1)].

Water: In clinical trials establishing the efficacy and safety of SAPHRIS, patients were instructed to avoid drinking for 10 minutes following sublingual dosing. The effect of water administration following 10 mg sublingual SAPHRIS dosing was studied at different time points of 2, 5, 10, and 30 minutes in 15 healthy male subjects. The exposure of asenapine following administration of water 10 minutes after sublingual dosing was equivalent to that when water was administered 30 minutes after dosing. Reduced exposure to asenapine was observed following water administration at 2 minutes (19% decrease) and 5 minutes (10% decrease) [see Dosage and Administration (2.1) and Patient Counseling Information (17.1)].

Special Populations:

Hepatic Impairment: The effect of decreased hepatic function on the pharmacokinetics of asenapine, administered as a single 5-mg sublingual dose, was studied in 30 subjects (8 each in those with normal hepatic function and Child-Pugh A and B groups, and 6 in the Child Pugh C group). In subjects with mild or moderate hepatic impairment (Child-Pugh A or B), asenapine exposure was 12% higher than that in subjects with normal hepatic function, indicating that dosage adjustment is not required for these subjects. In subjects with severe hepatic impairment, asenapine exposures were on average 7 times higher than the exposures of those in subjects with normal hepatic function. Thus, SAPHRIS is not recommended in patients with severe hepatic impairment (Child-Pugh C) [see Dosage in Specific Populations (2.4) and Use in Specific Populations (8.7) and Warnings and Precautions (5.14)].

Renal Impairment: The effect of decreased renal function on the pharmacokinetics of asenapine was studied in subjects with mildly (creatinine clearance (CrCl) 51 to 80 mL/min; N=8), moderately (CrCl 30 to 50 mL/min; N=8), and severely (CrCl less than 30 mL/min but not on dialysis; N=8) impaired renal function and compared to normal subjects (CrCl greater than 80 mL/min; N=8). The exposure of asenapine following a single dose of 5 mg was similar among subjects with varying degrees of renal impairment and subjects with normal renal function. Dosage adjustment based upon degree of renal impairment is not required. The effect of renal function on the excretion of other metabolites and the effect of dialysis on the pharmacokinetics of asenapine has not been studied [see Use in Specific Populations (8.6)].

Geriatric Patients: In elderly patients with psychosis (65–85 years of age), asenapine concentrations were on average 30 to 40% higher compared to younger adults. When the range of exposures in the elderly was examined, the highest exposure for asenapine was up to 2-fold higher than the highest exposure in younger subjects. In a population pharmacokinetic analysis, a decrease in clearance with increasing age was observed, implying a 30% higher exposure in elderly as compared to adult patients [see Use in Specific Populations (8.5)].

Gender: The potential difference in asenapine pharmacokinetics between males and females was not studied in a dedicated trial. In a population pharmacokinetic analysis, no significant differences between genders were observed.

Race: In a population pharmacokinetic analysis, no effect of race on asenapine concentrations was observed. In a dedicated study, the pharmacokinetics of SAPHRIS were similar in Caucasian and Japanese subjects.

13 NONCLINICAL TOXICOLOGY

13.1 Carcinogenesis, Mutagenesis, Impairment of Fertility

Carcinogenesis: In a lifetime carcinogenicity study in CD-1 mice asenapine was administered subcutaneously at doses up to those resulting in plasma levels (AUC) estimated to be 5 times those in humans receiving the MRHD of 10 mg twice daily. The incidence of malignant lymphomas was increased in female mice, with a no-effect dose resulting in plasma levels estimated to be 1.5 times those in humans receiving the MRHD. The mouse strain used has a high and variable incidence of malignant lymphomas, and the significance of these results to humans is unknown. There were no increases in other tumor types in female mice. In male mice, there were no increases in any tumor type.

In a lifetime carcinogenicity study in Sprague-Dawley rats, asenapine did not cause any increases in tumors when administered subcutaneously at doses up to those resulting in plasma levels (AUC) estimated to be 5 times those in humans receiving the MRHD.

Mutagenesis: No evidence for genotoxic potential of asenapine was found in the in vitro bacterial reverse mutation assay, the in vitro forward gene mutation assay in mouse lymphoma cells, the in vitro chromosomal aberration assays in human lymphocytes, the in vitro sister chromatid exchange assay in rabbit lymphocytes, or the in vivo micronucleus assay in rats.

Impairment of Fertility: Asenapine did not impair fertility in rats when tested at doses up to 11 mg/kg twice daily given orally. This dose is 10 times the maximum recommended human dose of 10 mg twice daily given sublingually on a mg/m^2 basis.

14 CLINICAL STUDIES

14.1 Schizophrenia

The efficacy of SAPHRIS in the treatment of schizophrenia in adults was evaluated in three fixed-dose, short-term (6 week), randomized, double-blind, placebo-controlled, and active-controlled (haloperidol, risperidone, and olanzapine) trials of adult patients who met DSM-IV criteria for schizophrenia and were having an acute exacerbation of their schizophrenic illness. In two of the three trials SAPHRIS demonstrated superior efficacy to placebo. In a third trial, SAPHRIS could not be distinguished from placebo; however, an active control in that trial was superior to placebo.

In the two positive trials for SAPHRIS, the primary efficacy rating scale was the Positive and Negative Syndrome Scale (PANSS), which assesses the symptoms of schizophrenia. The primary endpoint was change from baseline to endpoint on the PANSS total score. The results of the SAPHRIS trials in schizophrenia follow:

In trial 1, a 6-week trial (n=174), comparing SAPHRIS (5 mg twice daily) to placebo, SAPHRIS 5 mg twice daily was statistically superior to placebo on the PANSS total score.

In trial 2, a 6-week trial (n=448), comparing two fixed doses of SAPHRIS (5 mg and 10 mg twice daily) to placebo, SAPHRIS 5 mg twice daily was statistically superior to placebo on the PANSS total score. SAPHRIS 10 mg twice daily showed no added benefit compared to 5 mg twice daily and was not significantly different from placebo.

An examination of population subgroups did not reveal any clear evidence of differential responsiveness on the basis of age, gender or race.

Maintenance of efficacy has been demonstrated in a placebo-controlled, double-blind, multicenter, flexible dose (5 mg or 10 mg twice daily based on tolerability) clinical trial with a randomized withdrawal design. A total of 700 patients entered open-label treatment with SAPHRIS for a period of 26 weeks. Of these, a total of 386 patients who met pre-specified criteria for continued stability (mean length of stabilization was 22 weeks) were randomized to a double-blind, placebo-controlled, randomized withdrawal phase. SAPHRIS was statistically superior to placebo in time to relapse or impending relapse defined as increase in PANSS ≥20% from baseline and a Clinical Global Impression–Severity of Illness (CGI-S) score ≥4 (at least 2 days within 1 week) or PANSS score ≥5 on "hostility" or "uncooperativeness" items and CGI-S score >4 (>2 days within a week), or PANSS score ≥5 on any two of the following items: "unusual thought content," "conceptual disorganization," or "hallucinatory behavior" items, and CGI-S score ≥4 (≥2 days within 1 week) or investigator judgment of worsening symptoms or increased risk of violence to self (including suicide) or other persons. The Kaplan-Meier curves of the time to relapse or impending relapse during the double-blind, placebo-controlled, randomized withdrawal phase of this trial for SAPHRIS and placebo are shown in Figure 1.

14.2 Bipolar Disorder

Monotherapy: The efficacy of SAPHRIS in the treatment of acute mania was established in two similarly designed 3-week, randomized, double-blind, placebo-controlled, and active-controlled (olanzapine) trials of adult patients who met DSM-IV criteria for Bipolar I Disorder with an acute manic or mixed episode with or without psychotic features.

The primary rating instrument used for assessing manic symptoms in these trials was the Young Mania Rating Scale (YMRS). Patients were also assessed on the Clinical Global Impression – Bipolar (CGI-BP) scale. In both trials, all patients randomized to SAPHRIS were initially administered 10 mg twice daily, and the dose could be adjusted within the dose range of 5 to 10 mg twice daily from Day 2 onward based on efficacy and tolerability. Ninety percent of patients remained on the 10 mg twice daily dose. SAPHRIS was statistically superior to placebo on the YMRS total score and the CGI-BP Severity of Illness score (mania) in both studies.

An examination of subgroups did not reveal any clear evidence of differential responsiveness on the basis of age, gender or race.

Adjunctive Therapy: The efficacy of SAPHRIS as an adjunctive therapy in acute mania was established in a 12-week, placebo-controlled trial with a 3-week primary efficacy endpoint involving 326 patients with a manic or mixed episode of Bipolar I Disorder, with or without psychotic features, who were partially responsive to lithium or valproate monotherapy after at least 2 weeks of treatment. SAPHRIS was statistically superior to placebo in the reduction of manic symptoms (measured by the YMRS total score) as an adjunctive therapy to lithium or valproate monotherapy at week 3.

16 HOW SUPPLIED/STORAGE AND HANDLING

SAPHRIS (asenapine) sublingual tablets are supplied as:

5-mg Tablets

Round, white- to off-white sublingual tablets, with "5" on one side.

Child-resistant packaging
Box of 60 | 6 blisters with 10 tablets | NDC 0052-0118-06
Hospital Unit Dose
Box of 100 | 10 blisters with 10 tablets | NDC 0052-0118-90

10-mg Tablets

Round, white- to off-white sublingual tablets, with "10" on one side.

Child-resistant packaging
Box of 60 | 6 blisters with 10 tablets | NDC 0052-0119-06
Hospital Unit Dose
Box of 100 | 10 blisters with 10 tablets | NDC 0052-0119-90

5-mg Tablets, black cherry flavor

Round, white- to off-white sublingual tablets, with "5" on one side within a circle.

Child-resistant packaging
Box of 60 | 6 blisters with 10 tablets | NDC 0052-2139-03
Hospital Unit Dose
Box of 100 | 10 blisters with 10 tablets | NDC 0052-2139-04

10-mg Tablets, black cherry flavor

Round, white- to off-white sublingual tablets, with "10" on one side within a circle.

Child-resistant packaging
Box of 60 | 6 blisters with 10 tablets | NDC 0052-2142-03
Hospital Unit Dose
Box of 100 | 10 blisters with 10 tablets | NDC 0052-2142-04

Storage

Store at 15°–30°C (59°–86°F) [see USP Controlled Room Temperature].

17 PATIENT COUNSELING INFORMATION

17.1 Tablet Administration

[see Drug Interactions (7) and Clinical Pharmacology (12.3)].

17.2 Increased Mortality in Elderly Patients with Dementia-Related Psychosis

Patients and caregivers should be advised that elderly patients with dementia-related psychoses treated with atypical antipsychotic drugs are at increased risk of death compared with placebo. SAPHRIS is not approved for elderly patients with dementia-related psychosis [see Warnings and Precautions (5.1)].

17.3 Neuroleptic Malignant Syndrome

Patients and caregivers should be counseled that a potentially fatal symptom complex sometimes referred to as Neuroleptic Malignant Syndrome (NMS) has been reported in association with administration of antipsychotic drugs. Signs and symptoms of NMS include hyperpyrexia, muscle rigidity, altered mental status, and evidence of autonomic instability (irregular pulse or blood pressure, tachycardia, diaphoresis, and cardiac dysrhythmia) [see Warnings and Precautions (5.3)].

17.4 Hyperglycemia and Diabetes Mellitus

Patients should be aware of the symptoms of hyperglycemia (high blood sugar) and diabetes mellitus. Patients who are diagnosed with diabetes, those with risk factors for diabetes, or those that develop these symptoms during treatment should have their blood glucose monitored at the beginning of and periodically during treatment [see Warnings and Precautions (5.5)].

17.5 Weight Gain

Patients should be advised that they may experience weight gain. Patients should have their weight monitored regularly [see Warnings and Precautions (5.6)].

17.6 Orthostatic Hypotension

Patients should be advised of the risk of orthostatic hypotension (symptoms include feeling dizzy or lightheaded upon standing) especially early in treatment, and also at times of re-initiating treatment or increases in dose [see Warnings and Precautions (5.7)].

17.7 Leukopenia/Neutropenia

Patients with a pre-existing low WBC or a history of drug induced leukopenia/neutropenia should be advised that they should have their CBC monitored while taking SAPHRIS [see Warnings and Precautions (5.8)].

17.8 Interference with Cognitive and Motor Performance

Patients should be cautioned about performing activities requiring mental alertness, such as operating hazardous machinery or operating a motor vehicle, until they are reasonably certain that SAPHRIS therapy does not affect them adversely [see Warnings and Precautions (5.12)].

17.9 Heat Exposure and Dehydration

Patients should be advised regarding appropriate care in avoiding overheating and dehydration [see Warnings and Precautions (5.13)].

17.10 Concomitant Medication and Alcohol

Patients should be advised to inform their physicians if they are taking, or plan to take, any prescription or over-the-counter medications since there is a potential for interactions. Patients should be advised to avoid alcohol while taking SAPHRIS [see Drug Interactions (7)].

17.11 Pregnancy and Nursing

Patients should be advised to notify their physician if they become pregnant or intend to become pregnant during therapy with SAPHRIS. Patients should be advised not to breast feed if they are taking SAPHRIS [see Use in Special Populations (8.1, 8.3)].

Manufactured by: Catalent UK Swindon Zydis Ltd., Blagrove, Swindon, Wiltshire, SN5 8RU, UK

Distributed by: Schering Corporation, a subsidiary of MERCK & CO., INC., Whitehouse Station, NJ 08889, USA

U.S. Patent No. 5,763,476.

Copyright © 2009 N.V. Organon, a subsidiary of Merck & Co., Inc. All rights reserved.

xxxxx x/xx xx

SAPHRIS PACKAGE LABEL - 10mg/60 tablet carton

Rx only